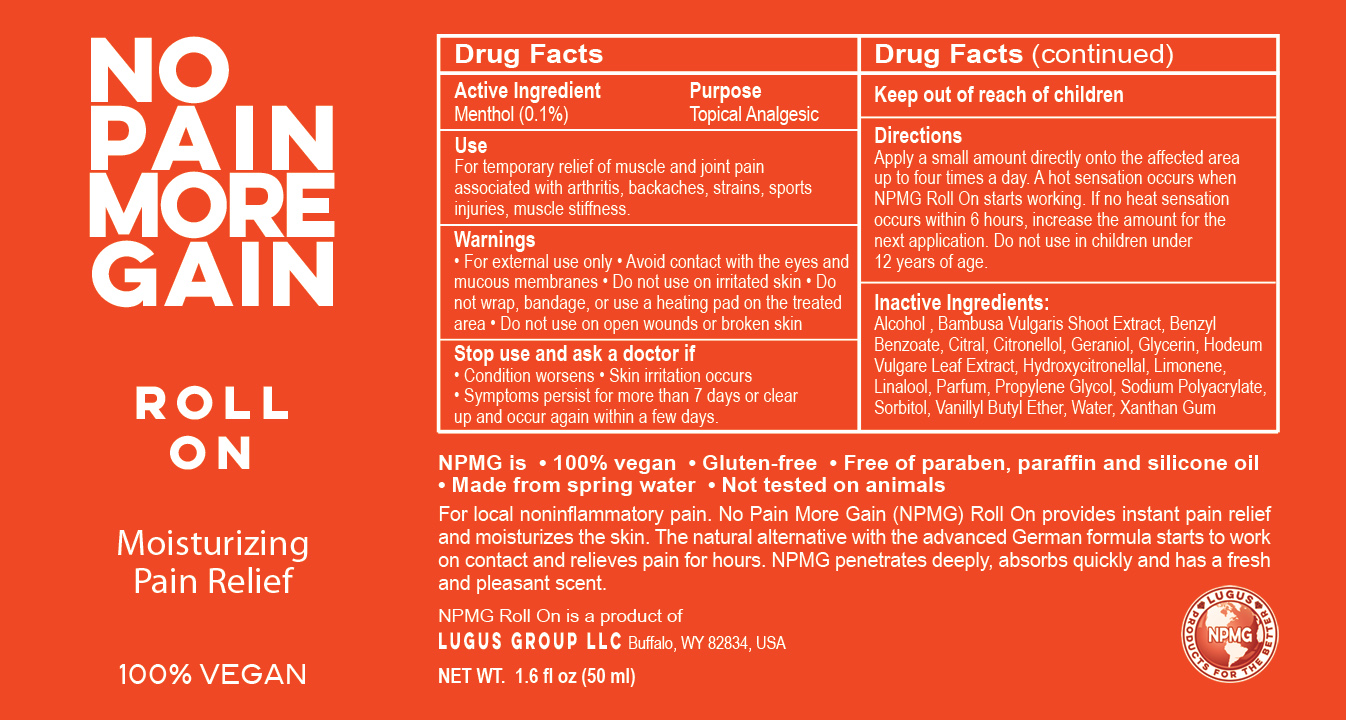 DRUG LABEL: No Pain More Gain
NDC: 69161-006 | Form: LIQUID
Manufacturer: Lugus Group LLC
Category: otc | Type: HUMAN OTC DRUG LABEL
Date: 20191217

ACTIVE INGREDIENTS: MENTHOL 10 mg/100 mg
INACTIVE INGREDIENTS: SODIUM POLYACRYLATE (2500000 MW); BAMBUSA VULGARIS STEM; HYDROXYCITRONELLAL; GERANIOL; BENZYL BENZOATE; LINALOOL, (-)-; ALCOHOL; GLYCERIN; HORDEUM VULGARE TOP; SORBITOL; LIMONENE, (+)-; WATER; CITRAL; PROPYLENE GLYCOL; .BETA.-CITRONELLOL, (R)-; VANILLYL BUTYL ETHER; XANTHAN GUM

Active Ingredient

Menthol (0.1%)

Purpose

Topical Analgesic

Use

For temporary relief of muscle and joint pain associated with arthritis, backaches, strains, sports injuries and muscle stiffness

Warnings

• For external use only • Avoid contact with the eyes and mucous membranes • Do not use on irritated skin • Do not wrap, bandage, or use a heating pad on the treated area • Do not use on open wounds or broken skin.

Stop use and ask a doctor if

• Condition worsens • skin irritation occurs • Symptoms persist for more than 7 days or clear up and occur again within a few days

Keep out of reach of children

Inactive Ingredients

Alcohol , Bambusa Vulgaris Shoot Extract, Benzyl Benzoate, Citral, Citronellol, Geraniol, Glycerin, Hodeum Vulgare Leaf Extract, Hydroxycitronellal, Limonene, Linalool, Parfum, Propylene Glycol, Sodium Polyacrylate, Sorbitol, Vanillyl Butyl Ether, Water, Xanthan Gum

INDICATIONS AND USAGE

100% Vegan

No Pain More Gain

Roll On

Moisturizing Pain Relief

NPMG is • 100% vegan • Gluten-free • Free of paraben, paraffin and silicone oil • Made from spring water • Not tested on animals

For local noninflammatory pain. No Pain More Gain (NPMG) Roll On provides instant pain relief and moisturizes the skin. The natural alternative with the advanced German formula starts to work on contact and relieves pain for hours. NPMG penetrates deeply, absorbs quickly and has a fresh and pleasant scent.

NPMG Roll On is a product of

Lugus Group LLC Buffalo, WY 82834, USA

NET WT. 1.6 fl oz (50 ml)

Directions

Apply a small amount directly onto the affected area up to four times a day. A hot sensation occurs when NPMG Roll On starts working. If no heat sensation occurs within 6 hours, increase the amount for the next application. Do not use in children under 12 years of age.